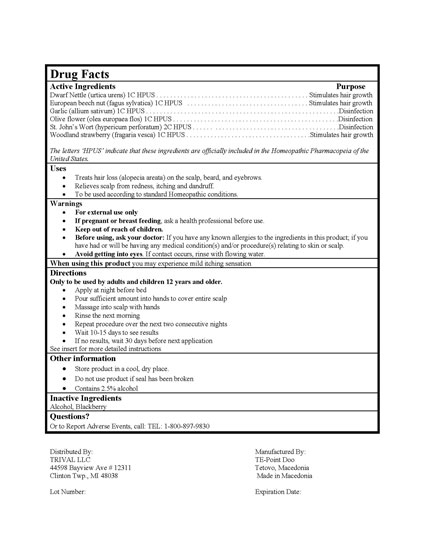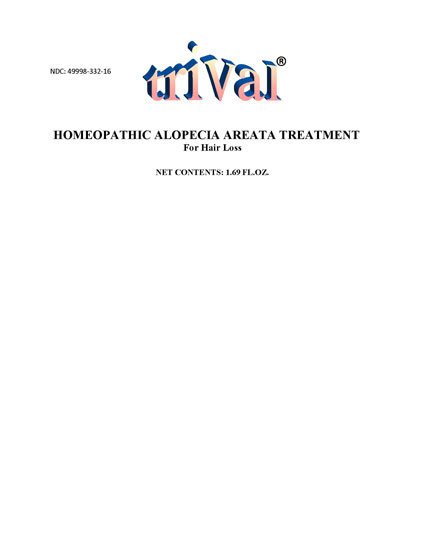 DRUG LABEL: Trival
NDC: 49998-332 | Form: TINCTURE
Manufacturer: TE-Point Doo
Category: homeopathic | Type: HUMAN OTC DRUG LABEL
Date: 20091222

ACTIVE INGREDIENTS: Urtica Urens 1 [hp_C]/1 1; Olea Europaea Flower 1 [hp_C]/1 1; St. John's Wort 2 [hp_C]/1 1; Fragaria Vesca Fruit 1 [hp_C]/1 1; Garlic 1 [hp_C]/1 1; Fagus Sylvatica Nut 1 [hp_C]/1 1
INACTIVE INGREDIENTS: Blackberry; Alcohol

PACKAGE LABEL

NDC: 49998-332-16
Trival
Homeopathic Alopecia Areata Treatment
For Hair Loss
1.69 FL. OZ.

DESCRIPTION

Distributed By:
TRIVAL LLC
44598 Bayview Ave #12311
Clinton Twp., MI 48038
Lot Number:
Manufactured By:
TE-Point Doo
Tetovo, Macedonia
Made in Macedonia
Expiration Date:

Drug Facts
Active Ingredients Purpose
Dwarf Nettle (urtica urens) 1C HPUS . . . . . . . . . . . Stimulates hair growth
European beech nut (fagus sylvatica) 1C HPUS . . . Stimulates hair growth
Garlic (allium sativum) 1C HPUS . . . . . . . . . . . . . . Disinfection
Olive flower (olea europaea flos) 1C HPUS . . . . . . . Disinfection
St. John's Wort (hypericum perforatum) 2C HPUS . . Disinfection
Woodland strawberry (fragaria vesca) 1C HPUS . . . Stimulates hair growth
The letters 'HPUS' indicate that these ingredients are officially included in the Homeopathic Pharmacopeia of the United States.

Uses
Treats hair loss (alopecia areata) on the scalp, beard, and eyebrows.
Relieves scalp from redness, itching and dandruff.
To be used according to standard Homeopathic conditions.

Warnings
For external use only
If pregnant or breast feeding, ask a health professional before use.
Keep out of reach of children.
Before using, ask your doctor: If you have any known allergies to the ingredients in this product; if you have had or will be having any medical condition(s) and/or procedure(s) relating to skin or scalp.
Avoid getting into eyes. If contact occurs, rinse with flowing water.

When using this product you may experience mild itching sensation.

Directions
Only to be used by adults and children 12 years and older
Apply at night before bed
Pour sufficient amount into hands to cover entire scalp
Massage into scalp with hands
Rinse the next morning
Repeat procedure over the next two consecutive nights
Wait 10-15 days to see results
If no results, wait 30 days before next application
See insert for more detailed instructions

Other information
Store product in a cool, dry place.
Do not use product if seal has been broken
Contains 2.5% alcohol

Inactive Ingredients
Alcohol, Blackberry

Questions?

Or to Report Adverse Events, call: TEL: 1-800-897-9830